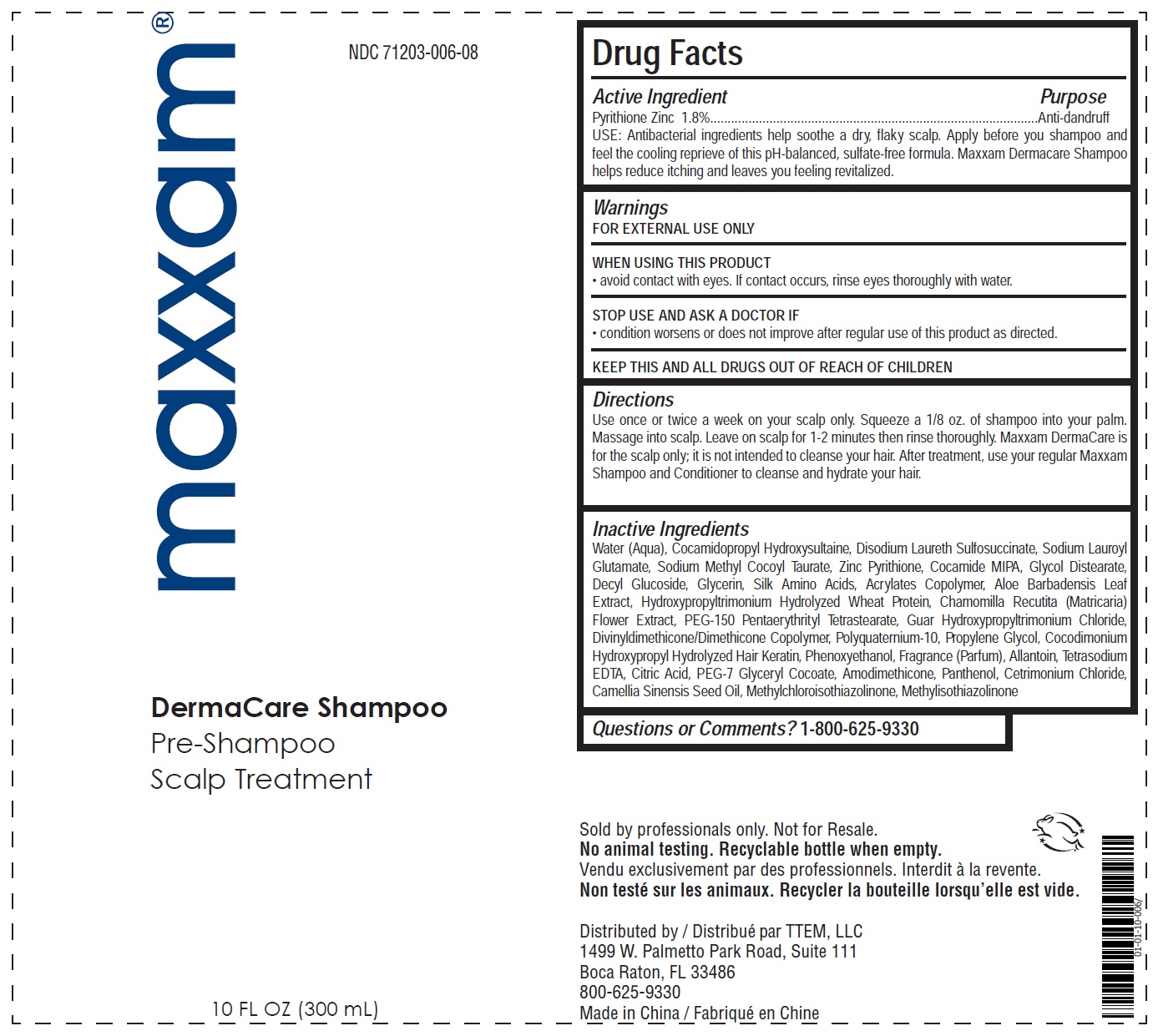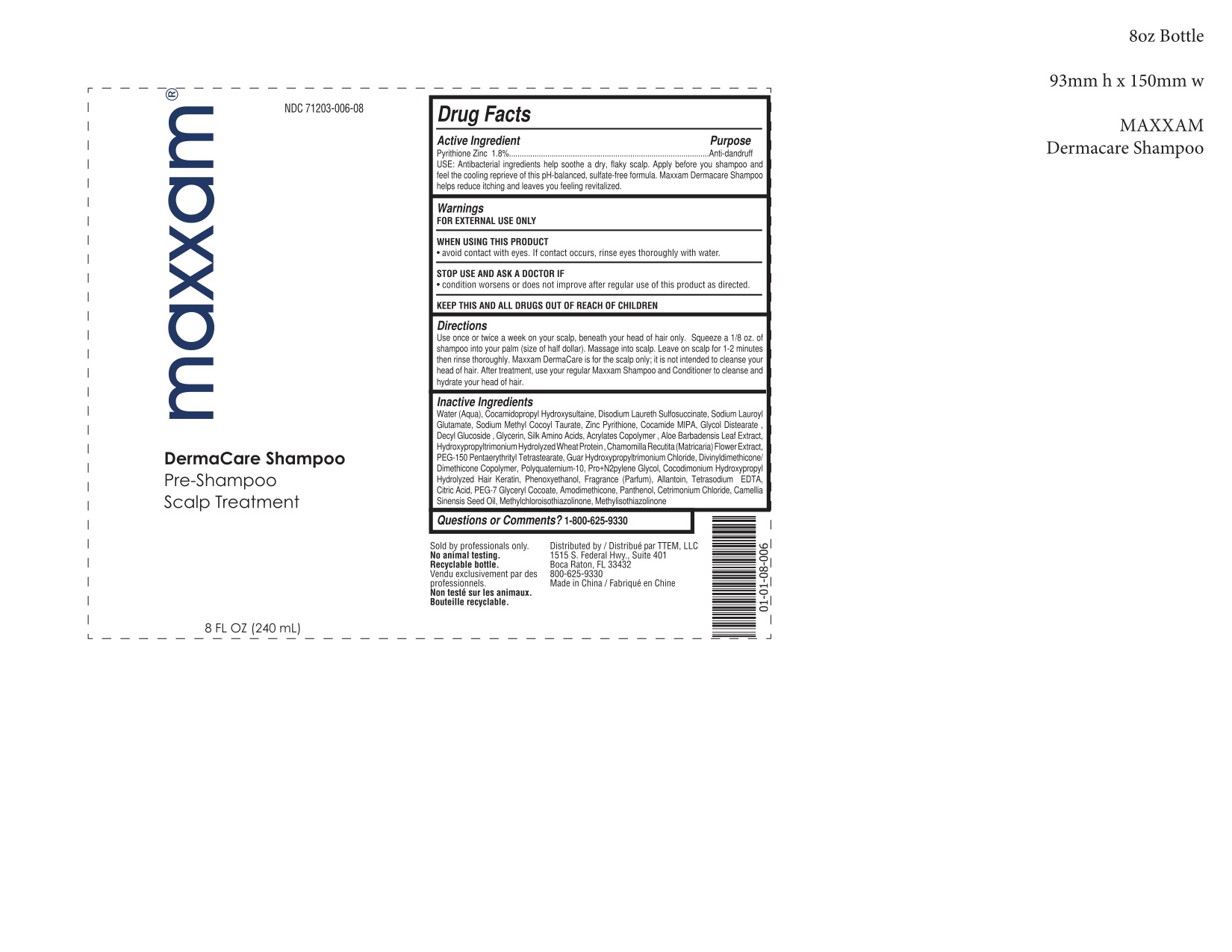 DRUG LABEL: maxxam dermaCare Pre-Shampoo Scalp Treatment
NDC: 71203-006 | Form: SHAMPOO
Manufacturer: EI GLOBAL GROUP LLC
Category: otc | Type: HUMAN OTC DRUG LABEL
Date: 20200819

ACTIVE INGREDIENTS: PYRITHIONE ZINC 1.8 g/100 mL
INACTIVE INGREDIENTS: COCO MONOISOPROPANOLAMIDE; GLYCERIN; CHAMOMILE; PEG-150 PENTAERYTHRITYL TETRASTEARATE; GUAR HYDROXYPROPYLTRIMONIUM CHLORIDE (1.7 SUBSTITUENTS PER SACCHARIDE); CAMELLIA SINENSIS SEED OIL; METHYLISOTHIAZOLINONE; AMINO ACIDS, SILK; ALOE VERA LEAF; EDETATE SODIUM; PEG-7 GLYCERYL COCOATE; CETRIMONIUM CHLORIDE; METHYLCHLOROISOTHIAZOLINONE; PHENOXYETHANOL; ALLANTOIN; CITRIC ACID MONOHYDRATE; PANTHENOL; WATER; COCAMIDOPROPYL HYDROXYSULTAINE; DISODIUM LAURETH SULFOSUCCINATE; SODIUM LAUROYL GLUTAMATE; SODIUM METHYL COCOYL TAURATE; GLYCOL DISTEARATE; DECYL GLUCOSIDE; BUTYL ACRYLATE/METHYL METHACRYLATE/METHACRYLIC ACID COPOLYMER (18000 MW); PROPYLENE GLYCOL; DIMETHICONE/VINYL DIMETHICONE CROSSPOLYMER (SOFT PARTICLE); AMINO ACIDS, HAIR KERATIN; POLYQUATERNIUM-10 (400 CPS AT 2%); HYDROLYZED WHEAT PROTEIN (ENZYMATIC, 3000 MW); AMODIMETHICONE (800 CST)

MAXXAM DermaCare Pre-shampoo Scalp Treatment

ACTIVE INGREDIENT

Pyrithione Zinc 1.8%

INACTIVE INGREDIENT

Water (Aqua), Cocamidopropyl Hydroxysultaine, Disodium Laureth Sulfosuccinate, Sodium Lauroyl Glutamate, Sodium Methyl Cocoyl Taurate, Zinc Pyrithione, Cocamide MIPA, Glycol Distearate , Decyl Glucoside , Glycerin, Silk Amino Acids, Acrylates Copolymer , Aloe Barbadensis Leaf Extract, Hydroxypropyltrimonium Hydrolyzed Wheat Protein, Chamomilla Recutita (Matricaria) Flower Extract, PEG-150 Pentaerythrityl Tetrastearate, Guar Hydroxypropyltrimonium Chloride, Divinyldimethicone/ Dimethicone Copolymer, Polyquatemium-10, Pro+N2pylene Glycol, Cocodimonium Hydroxypropyl Hydrolyzed Hair Keratin, Phenoxyethanol, Fragrance (Partum), Allantoin, Tetrasodium EDTA, Ctlric Acid, PEG-7 Glyceryl Cocoate, Amodimethicone, Panthenol, Cetrimonium Chloride, Camellia Sinensis Seed Oil, Methylchloroisothiazolinone, Methylisothiazolinone

DOSAGE AND ADMINISTRATION

Use: Anti-dandruff

Directions: Use once or twice a week on your scalp, beneath your head of hair only. Squeeze a 1/8 oz. of shampoo into your palm (size of half dollar). Massage into scalp. Leave on scalp for 1-2 minutes then rinse thoroughly. Maxxam DermaCare is for the scalp only; it is not intended to cleanse your head of hair. After treatment, use your regular Maxxam Shampoo and Conditioner to cleanse and hydrate your head of hair.

INDICATIONS AND USAGE

Use: Anti-dandruff

Directions: Use once or twice a week on your scalp, beneath your head of hair only. Squeeze a 1/8 oz. of shampoo into your palm (size of half dollar). Massage into scalp. Leave on scalp for 1-2 minutes then rinse thoroughly. Maxxam DermaCare is for the scalp only; it is not intended to cleanse your head of hair. After treatment, use your regular Maxxam Shampoo and Conditioner to cleanse and hydrate your head of hair.

WARNINGS

- For external use only
- When using this product avoid contact with eyes. If contact occurs, rinse eyes thoroughly with water.
- Stop use and ask a doctor if condition worsens or does not improve after regular use of this product as direct.

KEEP OUT OF REACH OF CHILDREN

KEEP THIS AND ALL DRUGS OUT OF REACH OF CHILDREN.

PURPOSE

Anti-dandruff